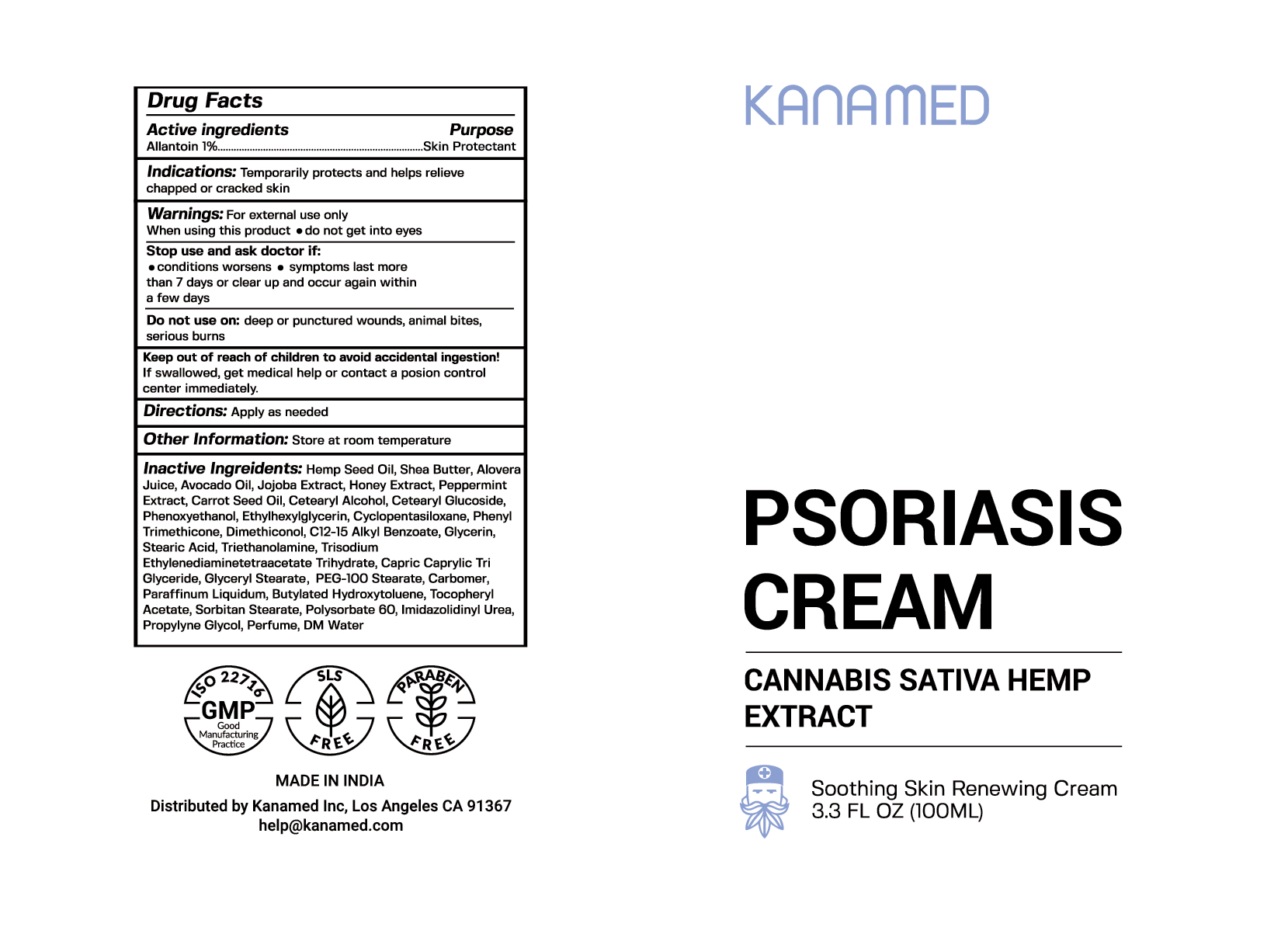 DRUG LABEL: Psoriasis Cream
NDC: 73239-1905 | Form: CREAM
Manufacturer: Kanamed Inc.
Category: otc | Type: HUMAN OTC DRUG LABEL
Date: 20191025

ACTIVE INGREDIENTS: ALLANTOIN 1 mg/100 mL
INACTIVE INGREDIENTS: ALOE VERA WHOLE; HEMP; WATER 1 mg/100 mL; PEPPERMINT

Psoriasis Cream

ACTIVE INGREDIENT

Allantoin 1%

INDICATIONS AND USAGE

Temporarily protects and helps relieve chapped or cracked skin

INACTIVE INGREDIENT

- Hemp seed oil
- Shea Butter
- Aloe vera Juice
- Avocado Oil
- Jojoba Extract
- Honey Extract
- Peppermint Extract
- Carrot Seed Oil
- Glycerine
- Stearic Acid
- EDTA
- Arcel 165
- Carbopol U-10,
- Cetyl Alcohol
- BHT
- Cetearyl Alcohol
- Cetearyl Glucoside
- Phenoxyethanol
- Ethylhexlglycerin
- Sorbitan Stearate
- Cyclopentasiloxane
- Phenyl Trimethicone
- Dimethiconol
- C12-15 Alkyl Benzoate
- Dimethicone Crosspolymer
- Caustic Soda/Sodium Hydroxide
- Capric Caprylic Triglyceride
- Polysorbate 60
- Ethylenediaminetetraacetic Acid
- Glycerine
- Carbopol U10
- Caustic Soda/Sodium hydroxide
- Propylene Glycol
- Sodium Benzonate
- DM Water
- Perfume
- Imidaolidnyl Urea

DOSAGE AND ADMINISTRATION

Apply as needed

WARNINGS

- For external use only
- When using this product do not get into eyes

STOP use and ask a doctor if:

- Conditions worsens
- symptoms last more than 7 days or clear up and occur again within a few days

Keep out of reach of children.

PURPOSE

Skin Protectant